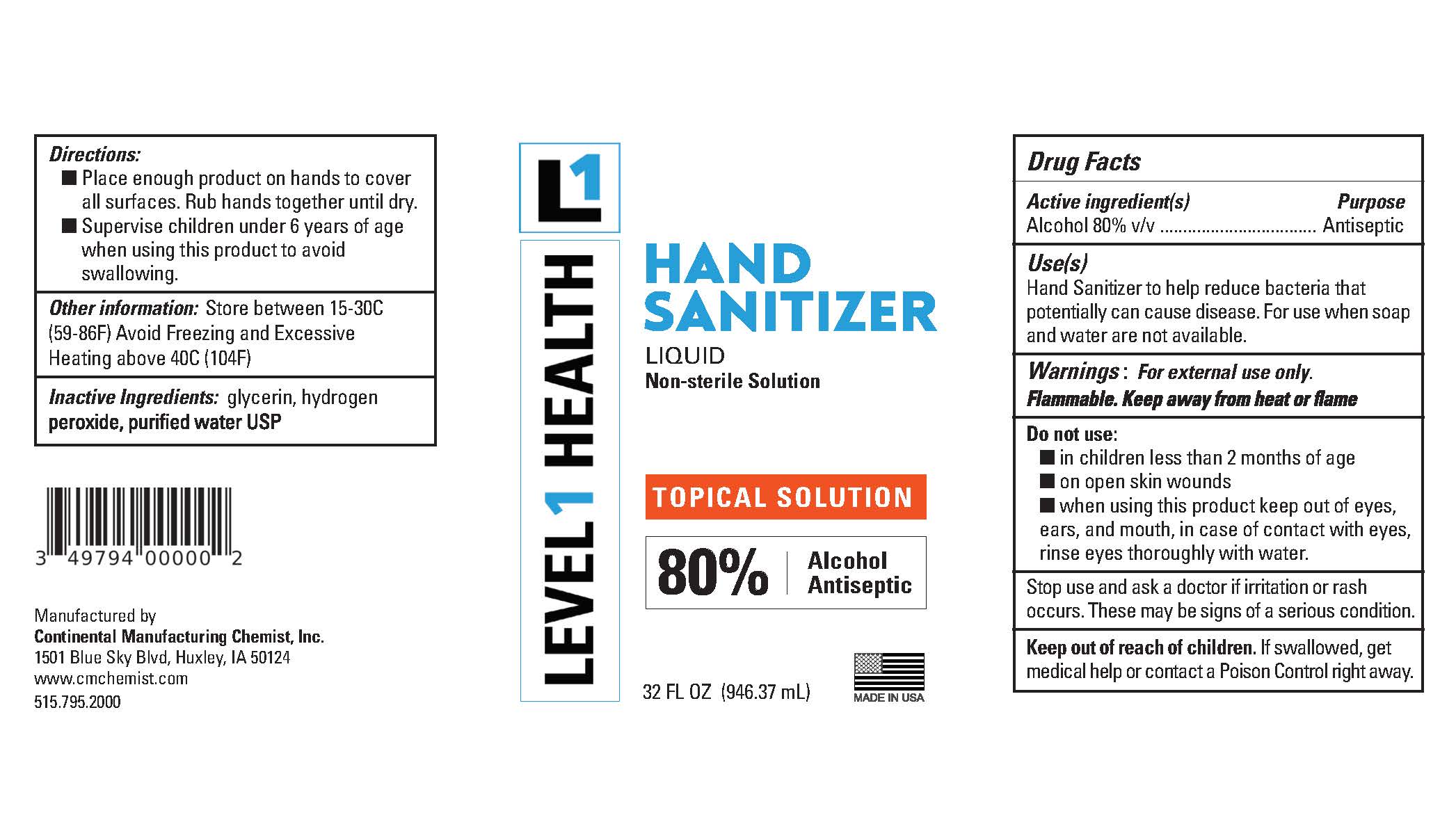 DRUG LABEL: Level 1 Health Hand Sanitizer Liquid Non-sterile Solution
NDC: 49794-002 | Form: LIQUID
Manufacturer: Continental Manufacturing Chemist, Inc.
Category: otc | Type: HUMAN OTC DRUG LABEL
Date: 20200513

ACTIVE INGREDIENTS: ALCOHOL 80 mL/100 mL
INACTIVE INGREDIENTS: GLYCERIN; WATER; HYDROGEN PEROXIDE

Drug Facts

Active Ingredient[s]

Alcohol 80% v/v

Purpose

Antiseptic

Use[s]

Hand sanitizer to help reduce bacteria that potentially can cause disease. For use when soap and water are not available.

Warnings

For external use only. Flammable. Keep away from heat or flame.

Do not use

- in children less than 2 months of age
- on open skin wounds

When using this product

keep out of eyes, ears, and mouth. In case of contact with eyes, rinse eyes thoroughly with water.

Stop use and ask a doctor

if irritation or rash occurs. These may be signs of a serious condition.

Keep out of reach of children.

If swallowed, get medical help or contact a Poison Control Center right away.

Direction

- Place enough product on hands to cover all surfaces. Rub hands together until dry.
- Supervise children under 6 years of age when using this product to avoid swallowing.

Other Information

- Store between 15o-30o C (59o 86oF)
- Avoid freezing and excessive heat above 40oC (104oF)

Inactive ingredients

glycerin, hydrogen peroxide, purified water USP

Principal Display Panel

Level 1 Health

Hand Sanitizer

Liquid

Non-Sterile Solution

Topical Solution

80% Alcohol Antiseptic

XX fl oz (X mL)

Manufactured by

Continental Manufacturing Chemist, Inc.

1501 Blue Sky Blvd, Huxley, IA 50124

www.cmchemist.com

515.795.2000

Made in USA

UPC Code